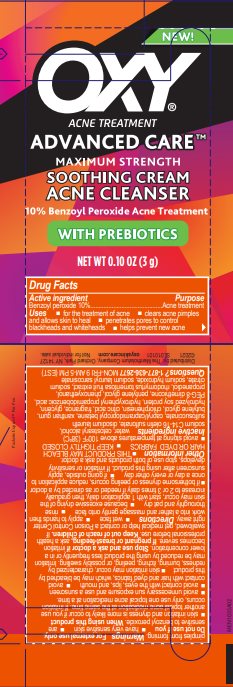 DRUG LABEL: OXY
NDC: 10742-1206 | Form: GEL
Manufacturer: The Mentholatum Company
Category: otc | Type: HUMAN OTC DRUG LABEL
Date: 20241213

ACTIVE INGREDIENTS: BENZOYL PEROXIDE 100 mg/1 g
INACTIVE INGREDIENTS: CETOSTEARYL ALCOHOL; WATER; SODIUM C14-16 OLEFIN SULFONATE; DISODIUM LAURETH SULFOSUCCINATE; CAPRYL/CAPRAMIDOPROPYL BETAINE; XANTHAN GUM; BUTYLENE GLYCOL; CHLORPHENESIN; ANHYDROUS CITRIC ACID; GLYCERIN; SOY PROTEIN; HYDROXYPHENYL PROPAMIDOBENZOIC ACID; PEG-8 DIMETHICONE; PENTYLENE GLYCOL; PHENOXYETHANOL; PROPANEDIOL; RHODOMYRTUS TOMENTOSA FRUIT; SODIUM CITRATE, UNSPECIFIED FORM; SODIUM HYDROXIDE; SODIUM LAUROYL SARCOSINATE

Drug Facts - OXY Advanced Care Soothing Cream Acne Cleanser

Active ingredient

Benzoyl peroxide 10%

Purpose

Acne treatment

Uses

- for the treatment of acne
- clears acne pimples and allows skin to heal
- penetrates pores to control blackheads and whiteheads
- helps prevent new acne pimples from forming

Warnings

For external use only

Do not use if you

- have very sensitive skin
- are sensitive to benzoyl peroxide

When using this product

- skin irritation and dryness is more likely to occur if you use another topical acne medication at the same time. If irritation occurs, only use one topical acne medication at a time.
- avoid unnecessary sun exposure and use a sunscreen
- avoid contact with eyes, lips, and mouth
- avoid contact with hair and dyed fabrics, which may be bleached by this product
- skin irritation may occur, characterized by redness, burning, itching, peeling, or possibly swelling. Irritation may be reduced by using the product less frequently or in a lower concentration.

Stop use and ask a doctor if

irritation becomes severe

If pregnant or breast-feeding,

ask a health professional before use.

Keep out of reach of children.

If swallowed, get medical help or contact a Poison Control Center right away.

Directions

- wet face
- apply to hands then work into a lather and massage gently onto face
- rinse thoroughly and pat dry
- because excessive drying of the skin may occur, start with 1 application daily, then gradually increase to 2 or 3 times daily if needed or as directed by a doctor
- if bothersome dryness or peeling occurs, reduce application to once a day or every other day
- if going outside, apply sunscreen after using this product. If irritation or sensitivity develops, stop use of both products and ask a doctor.

Other information

- THIS PRODUCT MAY BLEACH HAIR OR DYED FABRICS
- KEEP TIGHTLY CLOSED
- avoid storing at temperatures above 100°F (38°C)

Inactive ingredients

water, cetostearyl alcohol, sodium C14-16 olefin sulfonate, disodium laureth sulfosuccinate, capryl/capramidopropyl betaine, xanthan gum, butylene glycol, chlorphenesin, citric acid, fragrance, glycerin, hydrolyzed soy protein, hydroxyphenyl propamidobenzoic acid, PEG-8 dimethicone, pentylene glycol, phenoxyethanol, propanediol, rhodomyrtus tomentosa fruit extract, sodium citrate, sodium hydroxide, sodium lauroyl sarcosinate

Questions?

1-877-636-2677 MON-FRI 9 AM-5 PM (EST)